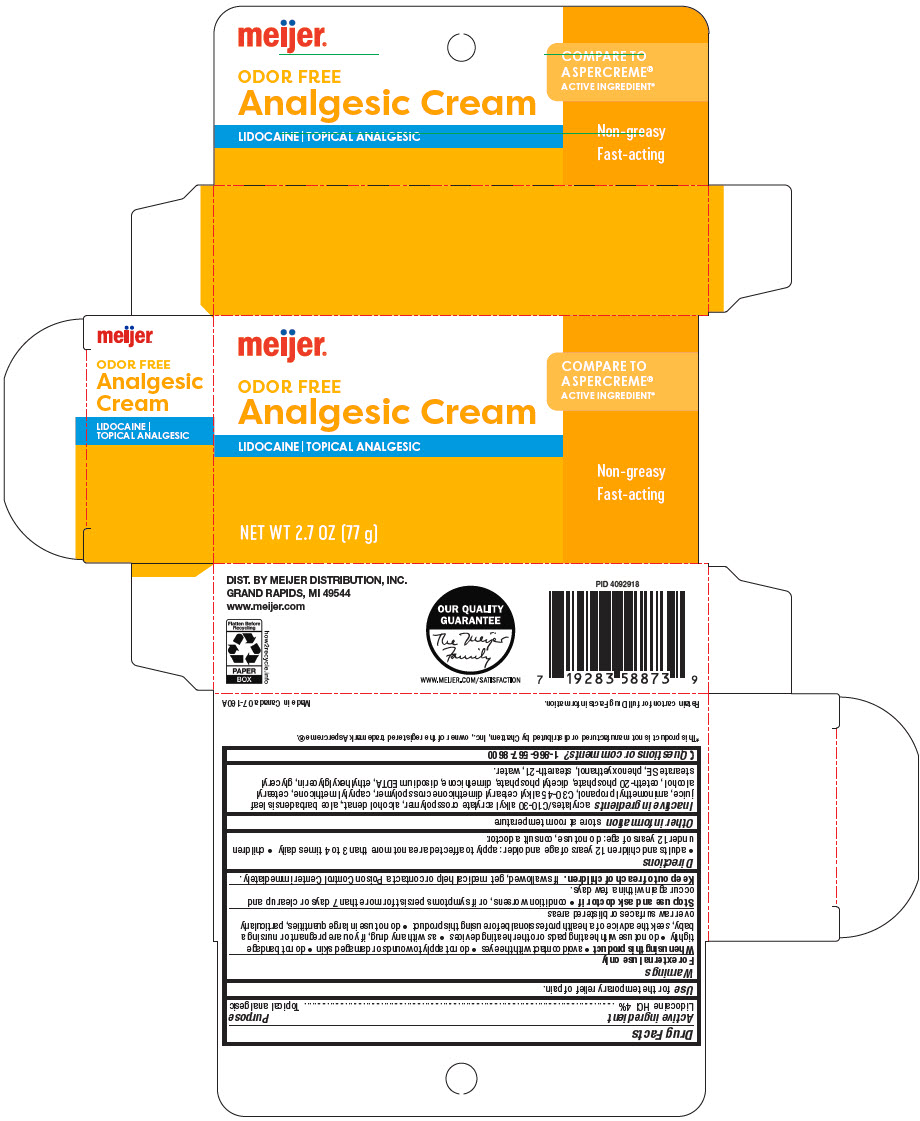 DRUG LABEL: Meijer Analgesic Lidocaine
NDC: 41250-518 | Form: CREAM
Manufacturer: Meijer Distribution, Inc
Category: otc | Type: HUMAN OTC DRUG LABEL
Date: 20240912

ACTIVE INGREDIENTS: LIDOCAINE HYDROCHLORIDE 40 mg/1 g
INACTIVE INGREDIENTS: CARBOMER INTERPOLYMER TYPE A (ALLYL SUCROSE CROSSLINKED); ALCOHOL; ALOE VERA LEAF; AMINOMETHYLPROPANOL; CAPRYLYL TRISILOXANE; CETOSTEARYL ALCOHOL; CETETH-20 PHOSPHATE; DIHEXADECYL PHOSPHATE; DIMETHICONE; EDETATE DISODIUM; ETHYLHEXYLGLYCERIN; GLYCERYL STEARATE SE; PHENOXYETHANOL; STEARETH-21; WATER

Meijer® Analgesic Cream Lidocaine 4%
Topical Analgesic

Drug Facts

Active ingredient

Lidocaine HCl 4%

Purpose

Topical analgesic

Uses

for the temporary relief of pain

Warnings

For external use only

When using this product

- avoid contact with eyes
- do not apply to wounds or damaged skin
- do not bandage tightly
- do not use with heating pads or other heating devices
- as with any drug, if you are pregnant or nursing a baby, seek the advice of a health professional before using this product
- do not use in large quantities, particularly over raw surfaces or blistered areas

Stop use and consult a doctor if condition worsens, or if symptoms persist for more than 7 days or clear up and occur again within a few days.

Keep out of reach of children. If swallowed, get medical help or contact a Poison Control Center immediately.

Directions

- adults and children 12 years of age and older: apply to affected area not more than 3 to 4 times daily
- children under 12 years of age: do not use, consult a doctor

Other information

store at room temperature

Inactive ingredients

Acrylates/C10-30 Alkyl Acrylate Crosspolymer, Alcohol denat., Aloe Barbadensis Leaf Juice, Aminomethyl Propanol, C30-45 Alkyl Cetearyl Dimethicone Crosspolymer, Caprylyl Methicone, Cetearyl Alcohol, Ceteth-20 Phosphate, Dicetyl Phosphate, Dimethicone, Disodium EDTA, Ethylhexylglycerin, Glyceryl Stearare SE, Phenoxyethanol, Steareth-21, Water.

Questions or comments?

1-866-567-8600

DIST. BY MEIJER
DISTRIBUTION, INC.
GRAND RAPIDS, MI 49544

PRINCIPAL DISPLAY PANEL - 77 g Bottle Carton

meijer®

ODOR FREE
Analgesic Cream

LIDOCAINE | TOPICAL ANALGESIC

NET WT 2.7 OZ (77 g)

COMPARE TO
ASPERCREME®
ACTIVE INGREDIENT*

Non-greasy
Fast-acting